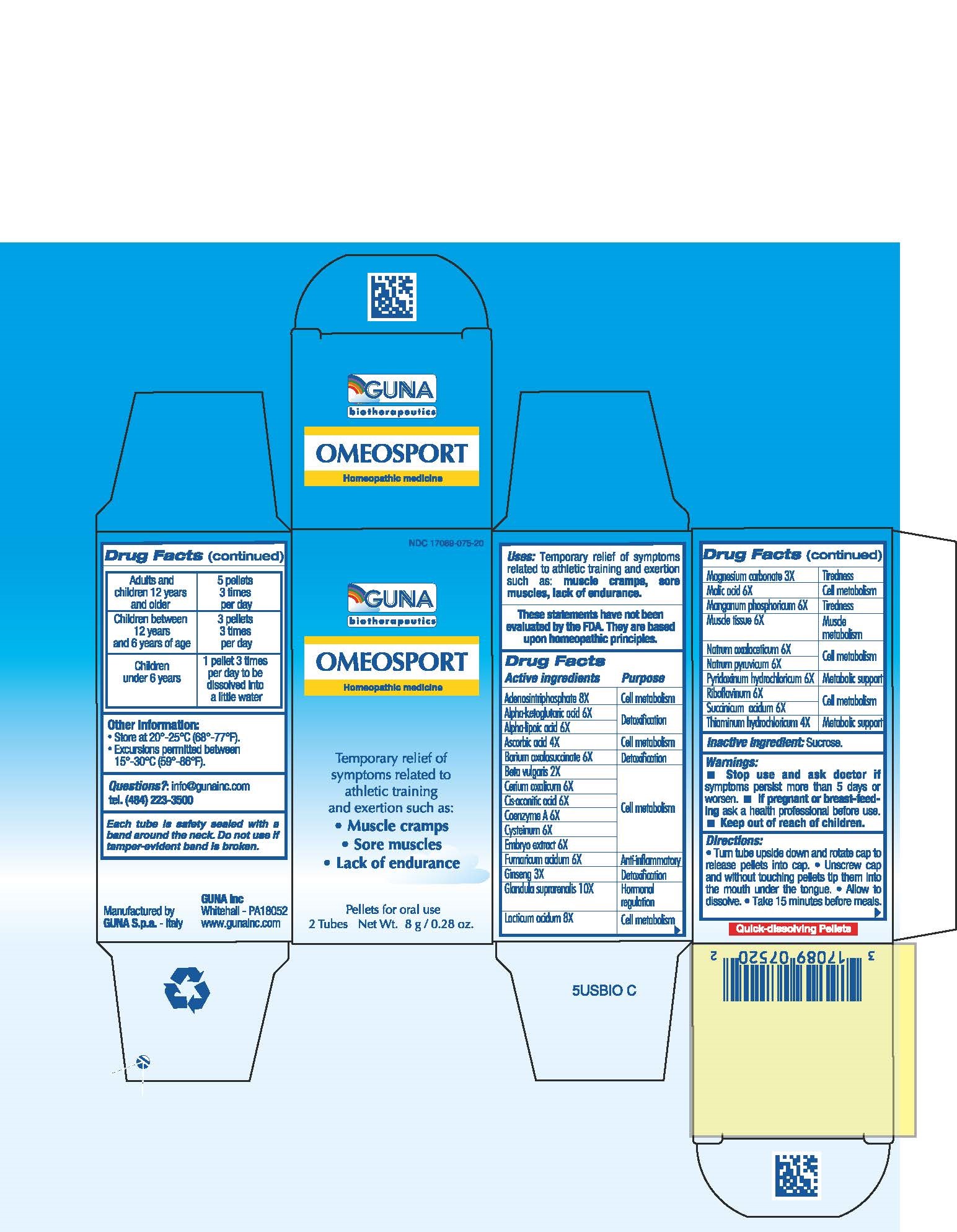 DRUG LABEL: OMEOSPORT
NDC: 17089-075 | Form: PELLET
Manufacturer: Guna spa
Category: homeopathic | Type: HUMAN OTC DRUG LABEL
Date: 20181221

ACTIVE INGREDIENTS: ADENOSINE TRIPHOSPHATE 8 [hp_X]/4 g; .ALPHA.-KETOGLUTARIC ACID 6 [hp_X]/4 g; .ALPHA.-LIPOIC ACID 6 [hp_X]/4 g; ASCORBIC ACID 4 [hp_X]/4 g; BARIUM OXALOSUCCINATE 6 [hp_X]/4 g; BEET 2 [hp_X]/4 g; CEROUS OXALATE NONAHYDRATE 6 [hp_X]/4 g; ACONITIC ACID, (Z)- 6 [hp_X]/4 g; COENZYME A 6 [hp_X]/4 g; CYSTEINE 6 [hp_X]/4 g; SUS SCROFA EMBRYO 6 [hp_X]/4 g; FUMARIC ACID 6 [hp_X]/4 g; ASIAN GINSENG 3 [hp_X]/4 g; SUS SCROFA ADRENAL GLAND 10 [hp_X]/4 g; LACTIC ACID 8 [hp_X]/4 g; MAGNESIUM CARBONATE 2 [hp_X]/4 g; MALIC ACID 6 [hp_X]/4 g; MANGANESE PHOSPHATE, DIBASIC 6 [hp_X]/4 g; PORK 6 [hp_X]/4 g; SODIUM DIETHYL OXALACETATE 6 [hp_X]/4 g; SODIUM PYRUVATE 6 [hp_X]/4 g; PYRIDOXINE HYDROCHLORIDE 6 [hp_X]/4 g; RIBOFLAVIN 6 [hp_X]/4 g; SUCCINIC ACID 6 [hp_X]/4 g; THIAMINE HYDROCHLORIDE 4 [hp_X]/4 g
INACTIVE INGREDIENTS: SUCROSE 3.5 g/4 g

OMEOSPORT

ACTIVE INGREDIENTS/PURPOSE

ADENOSINTRIPHOSPHATE 8X CELL METABOLISM
ALPHA-KETOGLUTARIC ACID 6X DETOXIFICATION
ALPHA-LIPOIC AC 6X DETOXIFICATION
ASCORBIC ACID 4X CELL METABOLISM
BARIUM OXALOSUCCINATE 6X DETOXIFICATION
BETA VULGARIS 2X CELL METABOLISM
CERIUM OXALICUM 6X CELL METABOLISM
CIS-ACONITIC ACID 6X CELL METABOLISM
COENZYME A 6X CELL METABOLISM
CYSTEINUM 6X CELL METABOLISM
EMBRYO EXTRACT 6X CELL METABOLISM
FUMARICUM ACIDUM 6X ANTI-INFLAMMATORY
GINSENG 3X DETOXIFICATION
GLANDULA SUPRARENALIS 10X HORMONAL REGULATION
LACTICUM ACIDUM 8X CELL METABOLISM
MAGNESIUM CARBONATE 2X TIREDNESS
MALIC ACID 6X CELL METABOLISM
MANGANUM PHOSPHORICUM 6X TIREDNESS
MUSCLE TISSUE 6X MUSCLE METABOLISM
NATRUM OXALACETICUM 6X CELL METABOLISM
NATRUM PYRUVICUM 6X CELL METABOLISM
PYRIDOXINUM HYDROCHLORICUM 6X METABOLIC SUPPORT
RIBOFLAVINUM 6X CELL METABOLISM
SUCCINICUM ACIDUM 6X CELL METABOLISM
THIAMINUM HYDROCHLORICUM 4X METABOLIC SUPPORT

USES

For the temporary relief of symptoms related to athletic training and exertion such as:

- Muscle cramps
- Sore muscles
- Lack of endurance

WARNINGS

Stop use and ask doctor if symptoms persist more than 5 days or worsen.
If pregnant or breast-feeding ask a health professional before use.
Keep out of reach of children.

PREGNANCY

If pregnant or breast-feeding ask a health professional before use.

WARNINGS

Keep out of reach of children

DIRECTIONS

Take 15 minutes before meals
Adults and children 12 years and older 5 pellets 3 times per day
Children between 12 years and 6 years of age 3 pellets 3 times per day
Children under 6 years 1 pellet 3 times per day to be dissolved into a little water

QUESTIONS

Questions?: info@gunainc.com
tel. (484) 223-3500

Inactive ingredient: Sucrose.

Directions:

- Turn tube upside down and rotate cap to release pellets into cap.
- Unscrew cap and without touching pellets tip them into the mouth under the tongue.
- Allow to dissolve
- Take 15 minutes before meals.